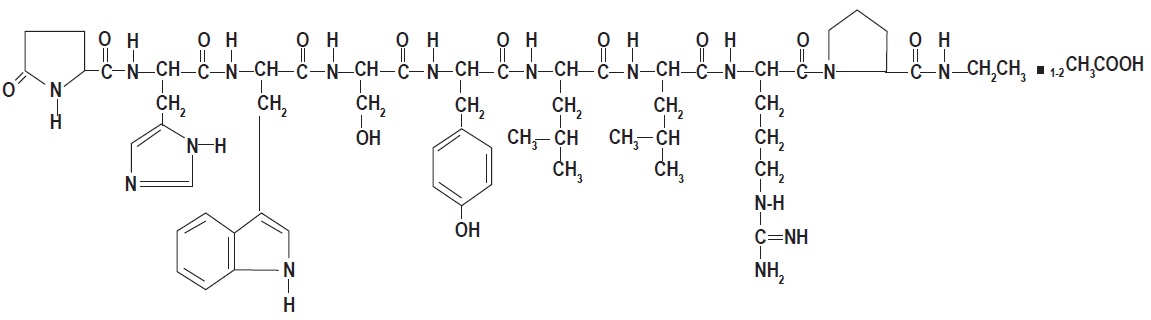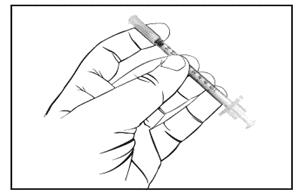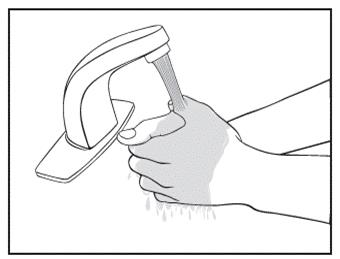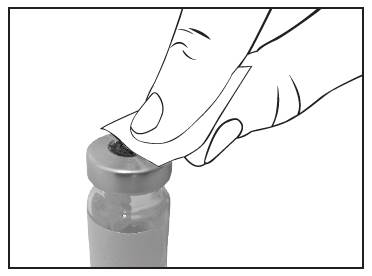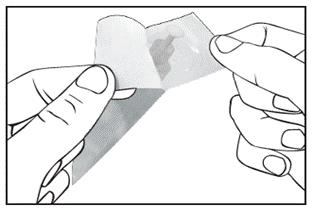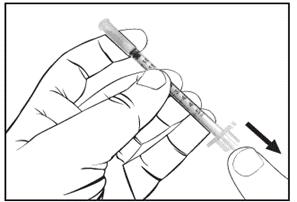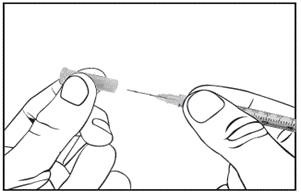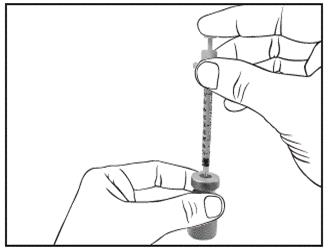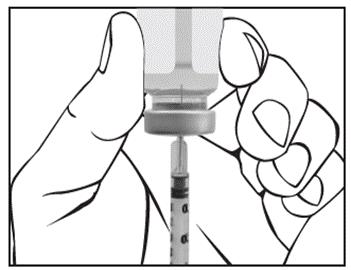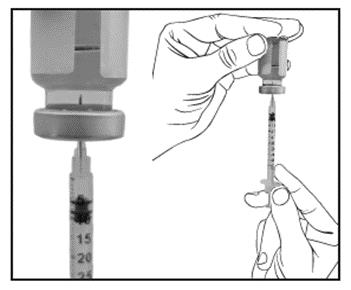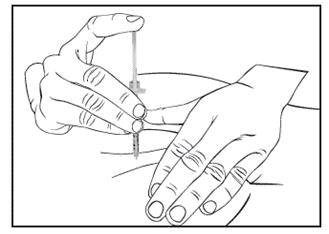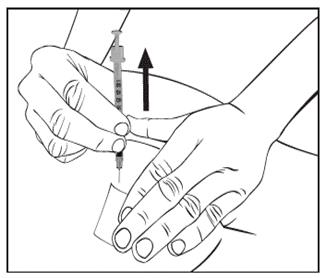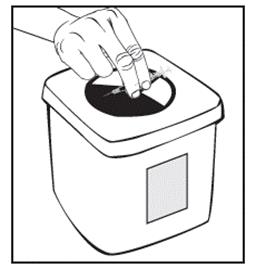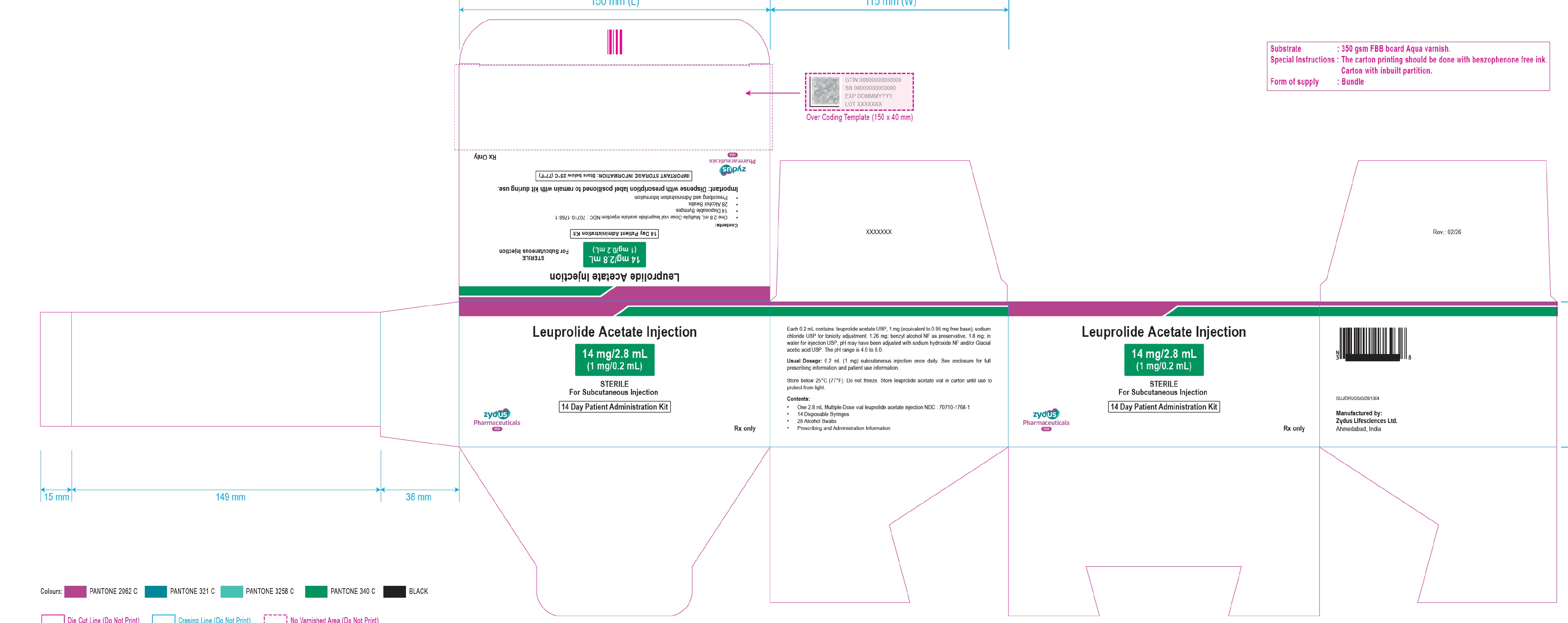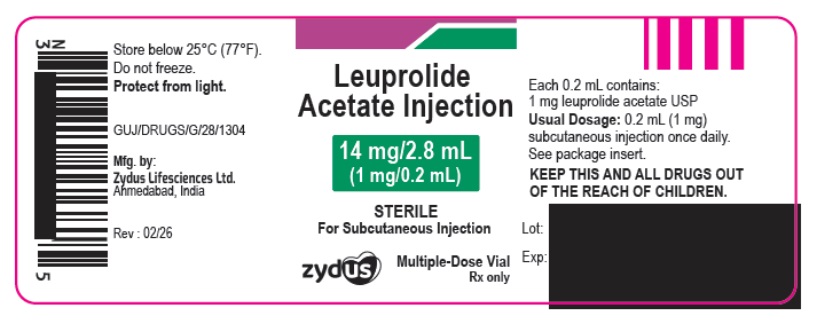 DRUG LABEL: LEUPROLIDE ACETATE

NDC: 70771-1687 | Form: KIT | Route: SUBCUTANEOUS
Manufacturer: Zydus Lifesciences Limited
Category: prescription | Type: HUMAN PRESCRIPTION DRUG LABEL
Date: 20260209

ACTIVE INGREDIENTS: LEUPROLIDE ACETATE 1 mg/0.2 mL; ISOPROPYL ALCOHOL 0.7 mL/1 mL
INACTIVE INGREDIENTS: ACETIC ACID; BENZYL ALCOHOL 1.8 mL/0.2 mL; SODIUM CHLORIDE 1.26 mg/0.2 mL; SODIUM HYDROXIDE; WATER; WATER

Leuprolide Acetate Injection
Rx only

DESCRIPTION

Leuprolide acetate, USP is a synthetic nonapeptide analog of naturally occurring gonadotropin releasing hormone (GnRH or LH-RH). The analog possesses greater potency than the natural hormone. The chemical name is 5-oxo-L-prolyl-L-histidyl-L-tryptophyl-L-seryl-L-tyrosyl-D-leucyl-L-leucyl-L-arginyl-N-ethyl-L-prolinamide acetate (salt) with the following structural formula:

Leuprolide Acetate Injection is a sterile, aqueous solution intended for subcutaneous injection. It is available in a 2.8 mL multiple-dose vial containing leuprolide acetate, USP (5 mg/mL), sodium chloride, USP (6.3 mg/mL) for tonicity adjustment, benzyl alcohol, NF as a preservative (9 mg/mL), and water for injection, USP. The pH may have been adjusted with sodium hydroxide, NF and/or Glacial acetic acid, USP.

CLINICAL PHARMACOLOGY

Leuprolide acetate, a GnRH agonist, acts as an inhibitor of gonadotropin secretion. Animal studies indicate that following an initial stimulation, continuous administration of leuprolide acetate results in suppression of ovarian and testicular steroidogenesis. This effect was reversible upon discontinuation of drug therapy. Administration of leuprolide acetate has resulted in inhibition of the growth of certain hormone dependent tumors (prostatic tumors in Noble and Dunning male rats and DMBA-induced mammary tumors in female rats) as well as atrophy of the reproductive organs.

In humans, subcutaneous administration of single daily doses of leuprolide acetate results in an initial increase in circulating levels of luteinizing hormone (LH) and follicle stimulating hormone (FSH), leading to a transient increase in levels of the gonadal steroids (testosterone and dihydrotestosterone in males, and estrone and estradiol in pre-menopausal females). However, continuous daily administration of leuprolide acetate results in decreased levels of LH and FSH. In males, testosterone is reduced to castrate levels. In pre-menopausal females, estrogens are reduced to post-menopausal levels. These decreases occur within two to four weeks after initiation of treatment, and castrate levels of testosterone in prostatic cancer patients have been demonstrated for periods of up to five years.

Leuprolide acetate is not active when given orally.

Pharmacokinetics

Absorption

Bioavailability by subcutaneous administration is comparable to that by intravenous administration.

Distribution

The mean steady-state volume of distribution of leuprolide following intravenous bolus administration to healthy male volunteers was 27 L. In vitro binding to human plasma proteins ranged from 43% to 49%.

Metabolism

In healthy male volunteers, a 1 mg bolus of leuprolide administered intravenously revealed that the mean systemic clearance was 7.6 L/h, with a terminal elimination half-life of approximately 3 hours based on a two compartment model. In rats and dogs, administration of ^14C-labeled leuprolide was shown to be metabolized to smaller inactive peptides, a pentapeptide (Metabolite I), tripeptides (Metabolites II and III) and a dipeptide (Metabolite IV). These fragments may be further catabolized.

The major metabolite (M-I) plasma concentrations measured in 5 prostate cancer patients reached maximum concentration 2 to 6 hours after dosing and were approximately 6% of the peak parent drug concentration. One week after dosing, mean plasma M-I concentrations were approximately 20% of mean leuprolide concentrations.

Excretion

Following administration of LUPRON DEPOT® 3.75 mg to 3 patients, less than 5% of the dose was recovered as parent and M-I metabolite in the urine.

Special Populations

The pharmacokinetics of the drug in hepatically and renally impaired patients has not been determined.

Drug Interactions

No pharmacokinetic-based drug-drug interaction studies have been conducted with leuprolide acetate. However, because leuprolide acetate is a peptide that is primarily degraded by peptidase and not by cytochrome P-450 enzymes as noted in specific studies, and the drug is only about 46% bound to plasma proteins, drug interactions would not be expected to occur.

CLINICAL STUDIES

In a controlled study comparing leuprolide acetate injection 1 mg/day given subcutaneously to DES (diethylstilbestrol), 3 mg/day, the survival rate for the two groups was comparable after two years of treatment. The objective response to treatment was also similar for the two groups.

INDICATIONS AND USAGE

Leuprolide acetate injection is indicated in the palliative treatment of advanced prostatic cancer.

CONTRAINDICATIONS

Leuprolide acetate injection is contraindicated in patients known to be hypersensitive to GnRH, GnRH agonist analogs or any of the excipients in leuprolide acetate injection: Reports of anaphylactic reactions to GnRH agonist analogs have been reported in the medical literature.

WARNINGS

Initially, leuprolide acetate injection, like other LH-RH agonists, causes increases in serum levels of testosterone. Transient worsening of symptoms, or the occurrence of additional signs and symptoms of prostate cancer, may develop during the first few weeks of leuprolide acetate injection treatment. Patients may experience a temporary increase in bone pain, which can be managed symptomatically. As with other LH-RH agonists, ureteral obstruction and spinal cord compression have been observed, which may contribute to paralysis with or without fatal complications.

Safe use of leuprolide acetate in pregnancy has not been established clinically. Leuprolide acetate injection may cause fetal harm.

Periodic monitoring of serum testosterone and prostate-specific antigen (PSA) levels is recommended, especially if the anticipated clinical or biochemical response to treatment has not been achieved. It should be noted that results of testosterone determinations are dependent on assay methodology. It is advisable to be aware of the type and precision of the assay methodology to make appropriate clinical and therapeutic decisions.

Severe Cutaneous Adverse Reactions

Leuprolide acetate can cause severe cutaneous adverse reactions (SCARs), including Stevens-Johnson syndrome/toxic epidermal necrolysis (SJS/TEN), drug reaction with eosinophilia and systemic symptoms (DRESS) and acute generalized exanthematous pustulosis (AGEP). SCARs, including SJS/TEN, DRESS, and AGEP, occurred in patients receiving leuprolide acetate; including cases with visceral involvement and/or requiring skin grafts [see Adverse Reactions].

Monitor patients for the development of SCARs.

If a SCAR is suspected, interrupt leuprolide acetate until the etiology of the reaction has been determined. Consultation with a dermatologist is recommended. If a SCAR is confirmed or for other grade 4 skin reactions, permanently discontinue leuprolide acetate.

PRECAUTIONS

Patients with metastatic vertebral lesions and/or with urinary tract obstruction should be closely observed during the first few weeks of therapy (see WARNINGSand ADVERSE REACTIONSsections).

Patients with known allergies to benzyl alcohol, an ingredient of the drug's vehicle, may present symptoms of hypersensitivity, usually local, in the form of erythema and induration at the injection site.

Hyperglycemia and an increased risk of developing diabetes have been reported in men receiving GnRH agonists. Hyperglycemia may represent development of diabetes mellitus or worsening of glycemic control in patients with diabetes. Monitor blood glucose and/or glycosylated hemoglobin (HbA1c) periodically in patients receiving a GnRH agonist and manage with current practice for treatment of hyperglycemia or diabetes.

Increased risk of developing myocardial infarction, sudden cardiac death and stroke has been reported in association with use of GnRH agonists in men. The risk appears low based on the reported odds ratios, and should be evaluated carefully along with cardiovascular risk factors when determining a treatment for patients with prostate cancer. Patients receiving a GnRH agonist should be monitored for symptoms and signs suggestive of development of cardiovascular disease and be managed according to current clinical practice.

Based on findings in animal studies, leuprolide acetate injection may cause fetal harm when administered to a pregnant woman. In animal developmental and reproductive toxicology studies, administration of the monthly formulation of leuprolide acetate on day 6 of pregnancy (sustained exposure was expected throughout the period of organogenesis) caused adverse embryo-fetal toxicity in animals at doses less than the human dose, based on body surface area, using an estimated daily dose. Advise pregnant patients and females of reproductive potential of the potential risk to the fetus.

Effect on QT/QTc Interval

Androgen deprivation therapy may prolong the QT/QTc interval. Providers should consider whether the benefits of androgen deprivation therapy outweigh the potential risks in patients with congenital long QT syndrome, congestive heart failure, frequent electrolyte abnormalities, and in patients taking drugs known to prolong the QT interval. Electrolyte abnormalities should be corrected. Consider periodic monitoring of electrocardiograms and electrolytes.

Information for Patients

See INFORMATION FOR PATIENTSwhich appears after the REFERENCEsection.

Laboratory Tests

Response to leuprolide acetate should be monitored by measuring serum levels of testosterone and prostate-specific antigen (PSA). In the majority of patients, testosterone levels increased above baseline during the first week, declining thereafter to baseline levels or below by the end of the second week of treatment. Castrate levels were reached within two to four weeks and once attained were maintained for as long as drug administration continued.

Drug Interactions

See CLINICAL PHARMACOLOGY, Pharmacokinetics section.

Drug/Laboratory Test Interactions

Administration of leuprolide acetate in therapeutic doses results in suppression of the pituitary-gonadal system. Normal function is usually restored within 4 to 12 weeks after treatment is discontinued.

Carcinogenesis, Mutagenesis, Impairment of Fertility

Two-year carcinogenicity studies were conducted with leuprolide acetate in rats and mice. In rats, a dose-related increase of benign pituitary hyperplasia and benign pituitary adenomas was noted at 24 months when the drug was administered subcutaneously at high daily doses (0.6 to 4 mg/kg). There was a significant but not dose-related increase of pancreatic islet-cell adenomas in females and of testicular interstitial cell adenomas in males (highest incidence in the low dose group). In mice, no pituitary abnormalities were observed at a dose as high as 60 mg/kg for two years. Patients have been treated with leuprolide acetate for up to three years with doses as high as 10 mg/day and for two years with doses as high as 20 mg/day without demonstrable pituitary abnormalities.

Mutagenicity studies have been performed with leuprolide acetate using bacterial and mammalian systems. These studies provided no evidence of a mutagenic potential.

Leuprolide injection may reduce male and female fertility. Administration of leuprolide acetate to male and female rats at dose of 0.024, 0.24, and 2.4 mg/kg as monthly depot formulation for up to 3 months (approximately as low as 1/30 of the human dose based on body surface area using an estimated daily dose in animals and humans) caused atrophy of the reproductive organs, and suppression of reproductive function. These changes were reversible upon cessation of treatment.

Pregnancy

Risk Summary

Based on findings in animal studies and mechanism of action, leuprolide acetate injection may cause fetal harm when administered to a pregnant woman. There are no available data in pregnant women to inform the drug-associated risk. In animal developmental and reproductive toxicology studies, administration of a monthly formulation of leuprolide acetate on day 6 of pregnancy (sustained exposure was expected throughout the period of organogenesis) caused adverse embryo-fetal toxicity in animals at doses less than the human dose based on body surface area using an estimated daily dose (see data). Advise pregnant patients and females of reproductive potential of the potential risk to the fetus.

Data

Animal Data

Major fetal malformations were observed in developmental and reproductive toxicology studies in rabbits after a single administration of the monthly formulation of leuprolide acetate administered on day 6 of pregnancy at test dosages of 0.00024, 0.0024, and 0.024 mg/kg (approximately 1/600 to 1/6 the human dose based on body surface area using an estimated daily dose in animals and humans). Since a depot formulation was utilized in the study, a sustained exposure to leuprolide was expected throughout the period of organogenesis and to the end of gestation. Similar studies in rats did not demonstrate an increase in fetal malformations, however, there was increased fetal mortality and decreased fetal weights with the two higher doses of the monthly formulation of leuprolide acetate in rabbits and with the highest dose in rats.

Lactation

The safety and efficacy of leuprolide acetate injection have not been established in females. There is no information regarding the presence of leuprolide in human milk, the effects on the breastfed child, or the effects on milk production. Because many drugs are excreted in human milk and because of the potential for serious adverse reactions in a breastfed child from leuprolide acetate injection, a decision should be made to discontinue breastfeeding or discontinue the drug, taking into account the importance of the drug to the mother.

Females and Males of Reproductive Potential

Infertility

Males

Based on findings in animals and mechanism of action, leuprolide acetate injection may impair fertility in males of reproductive potential.

Geriatric Use

In the clinical trials for leuprolide acetate injection, the majority (69%) of subjects studied were at least 65 years of age. Therefore, the labeling reflects the pharmacokinetics, efficacy and safety of leuprolide acetate injection in this population.

ADVERSE REACTIONS

Clinical Trials

In the majority of patients testosterone levels increased above baseline during the first week, declining thereafter to baseline levels or below by the end of the second week of treatment. This transient increase was occasionally associated with a temporary worsening of signs and symptoms, usually manifested by an increase in bone pain (see WARNINGSsection). Cases of temporary worsening of existing hematuria and urinary tract obstruction have occurred during the first week. Temporary weakness and paresthesia of the lower limbs have been reported.

Potential exacerbations of signs and symptoms during the first few weeks of treatment is a concern in patients with vertebral metastases and/or urinary obstruction which, if aggravated, may lead to neurological problems or increase the obstruction.

In a comparative trial of leuprolide acetate injection versus DES, in 5% or more of the patients receiving either drug, the following adverse reactions were reported to have a possible or probable relationship to drug as ascribed by the treating physician. Often, causality is difficult to assess in patients with metastatic prostate cancer. Reactions considered not drug related are excluded.

 | Leuprolide Acetate Injection (N=98) | DES (N=101)
 | Number of Reports
Cardiovascular System
Congestive heart failure | 1 | 5
ECG changes/ischemia | 19 | 22
High blood pressure | 8 | 5
Murmur | 3 | 8
Peripheral edema | 12 | 30
Phlebitis/thrombosis | 2 | 10
Gastrointestinal System
Anorexia | 6 | 5
Constipation | 7 | 9
Nausea/vomiting | 5 | 17
Endocrine System
*Decreased testicular size | 7 | 11
*Gynecomastia/breast tenderness or pain | 7 | 63
*Hot flashes | 55 | 12
*Impotence | 4 | 12
Hemic and Lymphatic System
Anemia | 5 | 5
Musculoskeletal System
Bone pain | 5 | 2
Myalgia | 3 | 9
Central/Peripheral Nervous System
Dizziness/lightheadedness | 5 | 7
General pain | 13 | 13
Headache | 7 | 4
Insomnia/sleep disorders | 7 | 5
Respiratory System
Dyspnea | 2 | 8
Sinus congestion | 5 | 6
Integumentary System
Dermatitis | 5 | 8
Urogenital System
Frequency/urgency | 6 | 8
Hematuria | 6 | 4
Urinary tract infection | 3 | 7
Miscellaneous
Asthenia | 10 | 10
* Physiologic effect of decreased testosterone.

In this same study, the following adverse reactions were reported in less than 5% of the patients on leuprolide acetate injection.

Cardiovascular System - Angina, Cardiac arrhythmias, Myocardial infarction, Pulmonary emboli

Gastrointestinal System - Diarrhea, Dysphagia, Gastrointestinal bleeding, Gastrointestinal disturbance, Peptic ulcer, Rectal polyps

Endocrine System - Libido decrease, Thyroid enlargement

Musculoskeletal System - Joint pain

Central/Peripheral Nervous System - Anxiety, Blurred vision, Lethargy, Memory disorder, Mood swings, Nervousness, Numbness, Paresthesia, Peripheral neuropathy, Syncope/blackouts, Taste disorders

Respiratory System - Cough, Pleural rub, Pneumonia, Pulmonary fibrosis

Integumentary System - Carcinoma of skin/ear, Dry skin, Ecchymosis, Hair loss, Itching, Local skin reactions, Pigmentation, Skin lesions

Urogenital System - Bladder spasms, Dysuria, Incontinence, Testicular pain, Urinary obstruction

Miscellaneous - Depression, Diabetes, Fatigue, Fever/chills, Hypoglycemia, Increased BUN, Increased calcium, Increased creatinine, Infection/inflammation, Ophthalmologic disorders, Swelling (temporal bone).

In an additional clinical trial and from long-term observation of both studies, the following additional adverse reactions were reported for patients receiving leuprolide acetate injection.

Cardiovascular System - Bradycardia, Carotid bruit, Extrasystole, Palpitations, Perivascular cuffing (eyes), Ruptured aortic aneurysm, Stroke, Tachycardia, Transient ischemic attack

Gastrointestinal System - Flatus, Dryness of mouth and throat, Hepatitis, Hepatomegaly, Occult blood (rectal exam), Rectal fistula/erythema

Endocrine System - Libido increase, Thyroid nodule

Musculoskeletal System - Ankylosing spondylosis, Arthritis, Blurred disc margins, Bone fracture, Muscle stiffness, Muscle tenderness, Pelvic fibrosis, Spasms/cramps

Central/Peripheral Nervous System - Auditory hallucinations/tinnitus, Decreased hearing, Decreased reflexes, Euphoria, Hyperreflexia, Loss of smell, Motor deficiency

Respiratory System - Chest tightness, Decreased breathing sounds, Hemoptysis, Pleuritic chest pain, Pulmonary infiltrate, Rales/rhonchi, Rhinitis, Strep throat, Wheezing/bronchitis

Integumentary System - Boil (pubic), Bruises, Hives, Keratosis, Mole, Shingles, Spiders

Urogenital System - Blisters on penis, Inguinal hernia, Penile swelling, Post void residual, Prostatic pain, Pyuria

Miscellaneous - Abdominal distention, Facial swelling/edema, Feet burning, Flu, Eyelid growth, Hypoproteinemia, Accidental injury, Knee effusion, Mass, Pallid, Sallow, Weakness.

Postmarketing

During postmarketing surveillance which includes other dosage forms and other patient populations, the following adverse reactions were reported.

Symptoms consistent with an anaphylactoid or asthmatic process have been rarely (incidence rate of about 0.002%) reported.

Symptoms consistent with fibromyalgia (e.g., joint and muscle pain, headaches, sleep disorders, gastrointestinal distress, and shortness of breath) have been reported individually and collectively.

Cardiovascular System - Hypotension, Myocardial infarction, Pulmonary embolism

Endocrine System - Diabetes

Gastrointestinal System - Hepatic dysfunction

Hepato-biliary disorder - Serious drug-induced liver injury

Hemic and Lymphatic System - Decreased WBC

Skin and Subcutaneous Tissue Disorders – Rash, Urticaria, Photosensitivity, Hair growth, SJS/TEN, DRESS, AGEP, Dermatitis exfoliative, Bullous dermatitis, Erythema multiforme;

Central/Peripheral Nervous System - Convulsion, Peripheral neuropathy, Spinal fracture/paralysis, Hearing disorder

Miscellaneous - Hard nodule in throat, Weight gain, Increased uric acid

Musculoskeletal System - Tenosynovitis-like symptoms

Respiratory System - Respiratory disorders, Interstitial lung disease

Urogenital System - Prostate pain.

General disorders and administration site conditions – injection site reactions including induration, abscess and necrosis.

Changes in Bone Density: Decreased bone density has been reported in the medical literature in men who have had orchiectomy or who have been treated with an LH-RH agonist analog. In a clinical trial, 25 men with prostate cancer, 12 of whom had been treated previously with leuprolide acetate for at least six months, underwent bone density studies as a result of pain. The leuprolide-treated group had lower bone density scores than the nontreated control group. It can be anticipated that long periods of medical castration in men will have effects on bone density.

Pituitary apoplexy: During post-marketing surveillance, rare cases of pituitary apoplexy (a clinical syndrome secondary to infarction of the pituitary gland) have been reported after the administration of gonadotropin-releasing hormone agonists. In a majority of these cases, a pituitary adenoma was diagnosed, with a majority of pituitary apoplexy cases occurring within 2 weeks of the first dose, and some within the first hour. In these cases, pituitary apoplexy has presented as sudden headache, vomiting, visual changes, ophthalmoplegia, altered mental status, and sometimes cardiovascular collapse. Immediate medical attention has been required.

See other LUPRON DEPOT® and leuprolide acetate injection package inserts for other events reported in the same and different patient populations.

OVERDOSAGE

In rats subcutaneous administration of 250 to 500 times the recommended human dose, expressed on a per body weight basis, resulted in dyspnea, decreased activity, and local irritation at the injection site. There is no evidence at present that there is a clinical counterpart of this phenomenon. In early clinical trials with leuprolide acetate doses as high as 20 mg/day for up to two years caused no adverse effects differing from those observed with the 1 mg/day dose.

DOSAGE AND ADMINISTRATION

The recommended dose is 1 mg (0.2 mL or 20 unit mark) administered as a single daily subcutaneous injection. As with other drugs administered chronically by subcutaneous injection, the injection site should be varied periodically. Each 0.2 mL contains 1 mg of leuprolide acetate, USP, sodium chloride, USP for tonicity adjustment, 1.8 mg of benzyl alcohol, NF as preservative and water for injection, USP. The pH may have been adjusted with sodium hydroxide, NF and/or Glacial acetic acid, USP.

Follow the pictorial directions on the reverse side of this package insert for administration.

NOTE: As with all parenteral products, inspect the solution for discoloration and particulate matter before each use.

HOW SUPPLIED

Leuprolide Acetate Injection is a sterile solution supplied in a 2.8 mL multiple-dose vial. The vial is packaged as follows: 14 Day Patient Administration Kit with 14 disposable syringes and 28 alcohol swabs, NDC 70771-1687-3.

Store below 77°F (25°C). Do not freeze. Protect from light; store vial in carton until use.

REFERENCES

1. "OSHA Hazardous Drugs." OSHA. http://www.osha.gov/SLTC/hazardousdrugs/index.html

INFORMATION FOR PATIENTS

Be sure to consult your physician with any questions you may have or for information about leuprolide acetate injection and its use.

WHAT IS LEUPROLIDE ACETATE INJECTION?

Leuprolide acetate injection is chemically similar to gonadotropin releasing hormone (GnRH or LH-RH) a hormone which occurs naturally in your body. Normally, your body releases small amounts of LH-RH and this leads to events which stimulate the production of sex hormones.

However, when you inject leuprolide acetate injection, the normal events that lead to sex hormone production are interrupted and testosterone is no longer produced by the testes.

Leuprolide acetate injection must be injected because, like insulin which is injected by diabetics, leuprolide acetate is inactive when taken by mouth.

If you were to discontinue the drug for any reason, your body would begin making testosterone again.

DIRECTIONS FOR USING LEUPROLIDE ACETATE INJECTION

1. Wash hands thoroughly with soap and water.
2. When using a new vial of leuprolide acetate injection, flip off the plastic cover to expose the grey rubber stopper. Wipe metal ring and rubber stopper with an alcohol wipe each time you use leuprolide acetate injection. Check the liquid in the vial for particulate matter and discoloration prior to use. DO NOT USE if the liquid is not clear or has particles and replace with a new vial.
3. Remove needle cap and inject the needle in the center of the rubber stopper on the leuprolide acetate injection vial.
4. Take cover off needle. Push the needle through the center of the rubber stopper on the leuprolide acetate injection vial.
5. Push the plunger all the way in to inject air into the vial.
6. Keep the needle in the vial and turn the vial upside down. Check to make sure the tip of the needle is in the liquid. Slowly pull back on the plunger, until the syringe fills to the 0.2 mL or 20 unit mark.
7. Toward the end of a two-week period, the amount of leuprolide acetate injection left in the vial will be small. Take special care to hold the vial straight and to keep the needle tip in liquid while pulling back on the plunger.
8. Keeping the needle in the vial and the vial upside down, check for air bubbles in the syringe. If you see any, push the plunger slowly in to push the air bubble back into the vial. Keep the tip of the needle in the liquid and pull the plunger back again to fill to the 0.2 mL or 20 unit mark.
9. Do this again if necessary to eliminate air bubbles.
10. To protect your skin, inject each daily dose at a different injection site.
11. Choose an injection site. Cleanse the injection site with another alcohol wipe.
12. Hold the syringe in one hand. Hold the skin taut, or pull up a little flesh with the other hand, as you were instructed.
13. Holding the syringe as you would a pencil, inject the needle all the way into the skin at a 90° angle. Push the plunger to administer the injection.
14. Hold an alcohol wipe down on your skin where the needle is inserted and withdraw the needle at the same angle it was inserted.
15. Use the disposable syringe only once and dispose of it properly as you were instructed. Needles thrown into a garbage bag could accidentally stick someone. NEVER LEAVE SYRINGES OR DRUGS WHERE CHILDREN CAN REACH THEM.

SOME SPECIAL ADVICE

- You may experience hot flashes when using leuprolide acetate injection. During the first few weeks of treatment you may experience increased bone pain, increased difficulty in urinating, and less commonly but most importantly, you may experience the onset or aggravation of nerve symptoms. In any of these events, discuss the symptoms with your doctor. Like other treatment options, leuprolide acetate injection may cause impotence. Notify your doctor if you develop new or worsened symptoms after beginning leuprolide acetate injection treatment.
- You may experience some irritation at the injection site, such as burning, itching or swelling. These reactions are usually mild and go away. If they do not, tell your doctor.
- If you have experienced an allergic reaction to other drugs like leuprolide acetate injection, you should not use this drug.
- Do not stop taking your injections because you feel better. You need an injection every day to make sure leuprolide acetate injection keeps working for you.
- If you need to use an alternate to the syringe supplied with leuprolide acetate, low-dose insulin syringes should be utilized.
- When the drug level gets low, take special care to hold the vial straight up and down and to keep the needle tip in liquid while pulling back on the plunger.
- Do not try to get every last drop out of the vial. This will increase the possibility of drawing air into the syringe and getting an incomplete dose. Some extra drug has been provided so that you can withdraw the recommended number of doses.
- Tell your pharmacist when you will need leuprolide acetate injection so it will be at the pharmacy when you need it.
- Store below 77°F (25°C). Do not store near a radiator or other very warm place. Do not freeze. Protect from light; store vial in carton until use.
- Do not leave your drug or hypodermic syringes where anyone can pick them up.
- Keep this and all other medications out of reach of children.

Brands listed are the trademarks of their respective owners.

Manufactured by
Zydus Lifesciences Ltd.
Ahmedabad, India

Rev.: 10/25

PATIENT INFORMATION

INSTRUCTIONS FOR USE

Leuprolide Acetate (loo' proe lide as' e tate) Injection

Read the Instructions for Use before you start using leuprolide acetate injection and each time you get a refill. There may be new information. This information does not take the place of talking to your doctor about your medical condition or your treatment. Your doctor should show you how to draw up leuprolide acetate injection and give the injection the right way before you inject the first time.

Do not share your syringes with other people. You may give other people a serious infection or get a serious infection from them.

Supplies you will need for the leuprolide acetate injection:

- 1 vial of leuprolide acetate injection
- a sterile 1/2 mL syringe with a 28 gauge, 1/2 inch sterile needle attached (See Figure A)
- 1 cotton gauze
- 2 alcohol swabs
- 1 puncture resistant sharps container (See "Disposal of used syringes and vials")

Figure A

Preparing the leuprolide acetate injection

Step 1.

Wash hands thoroughly (See Figure B) and dry them with a clean towel.

Figure B

Step 2.

- Check the liquid in the vial. It should look clear. Do not use if it is not clear or if it has particles in it.
- If using a new vial, flip off the plastic cover to expose the grey rubber stopper.
- Use an alcohol swab to clean the metal ring and the grey rubber stopper on the medicine vial every day, just before you use it (See Figure C).

Figure C

Step 3.

Remove outer wrapping from 1 syringe (See Figure D).

Figure D

Step 4.

Pull the syringe plunger back until the tip is at the proper mark for the prescribed dose (See Figure E).

Figure E

Step 5.

Uncover needle by pulling the cap straight off (See Figure F). Do not touch the needle.

Figure F

Step 6.

- Place the vial on a clean flat surface.
- Inject the needle through the center of the rubber stopper on the vial (See Figure G).
- Push the plunger all the way in to inject air into the vial.

Figure G

Step 7.

- Keep the needle in the vial.
- Lift the vial and turn it straight upside down.
- Check to see that the needle tip is in the liquid (See Figure H).

Figure H

Step 8.

- With the needle tip still in the liquid, slowly pull back the plunger until syringe fills to the proper mark (See Figure I).
- If any bubbles appear in the syringe, remove them by pushing the plunger up slowly.

Figure I

Giving leuprolide acetate injection

Step 9.

- Choose a different injection site each day.
- Clean the injection site with a new alcohol swab.
- Hold the skin fold between your thumb and your index finger or as you were instructed by your doctor.
- Inject the needle straight into the skin quickly, as shown by your doctor in a 90° angle (See Figure J).
- Push the plunger to inject the medicine.

Figure J

Step 10.

- Remove the needle at the same angle it was inserted (90°) (See Figure K).
- Wipe the skin with a cotton gauze.

Figure K

Disposal of used syringes and vial

Step 11.

- Put the used syringes and vials in a FDA-cleared sharps disposal container right away after use (See Figure L). Do not throw away (dispose of) loose syringes or vials in your household trash.
- If you do not have a FDA-cleared sharps disposal container, you may use a household container that is:
  - made of a heavy-duty plastic,
  - can be closed with a tight-fitting, puncture-resistant lid, without sharps being able to come out,
  - upright and stable during use,
  - leak-resistant, and
  - properly labeled to warn of hazardous waste inside the container.
- When your sharps disposal container is almost full, you will need to follow your community guidelines for the right way to dispose of your sharps disposal container. There may be state or local laws about how you should throw away used syringes and vials. For more information about safe sharps disposal, and for specific information about sharps disposal in the state that you live in, go to the FDA's website at: http://www.fda.gov/safesharpsdisposal.
- Do not dispose of your used sharps disposal container in your household trash unless your community guidelines permit this. Do not recycle your used sharps disposal container.

Figure L

Manufactured by
Zydus Lifesciences Ltd.
Ahmedabad, India

Rev.: 10/25

This Instructions for Use has been approved by the U.S. Food and Drug Administration

PACKAGE LABEL.PRINCIPAL DISPLAY PANEL

NDC 70771-1687-3

Leuprolide Acetate Injection, 14 mg/2.8 mL (1 mg/0.2 mL)

Sterile

For Subcutaneous Injection

14 Day Patient Administration Kit

Rx only

NDC 70771-1686-1

Leuprolide Acetate Injection, 14 mg/2.8 mL (1 mg/0.2 mL)

Sterile

For Subcutaneous Injection

Multiple-Dose Vial

Rx only